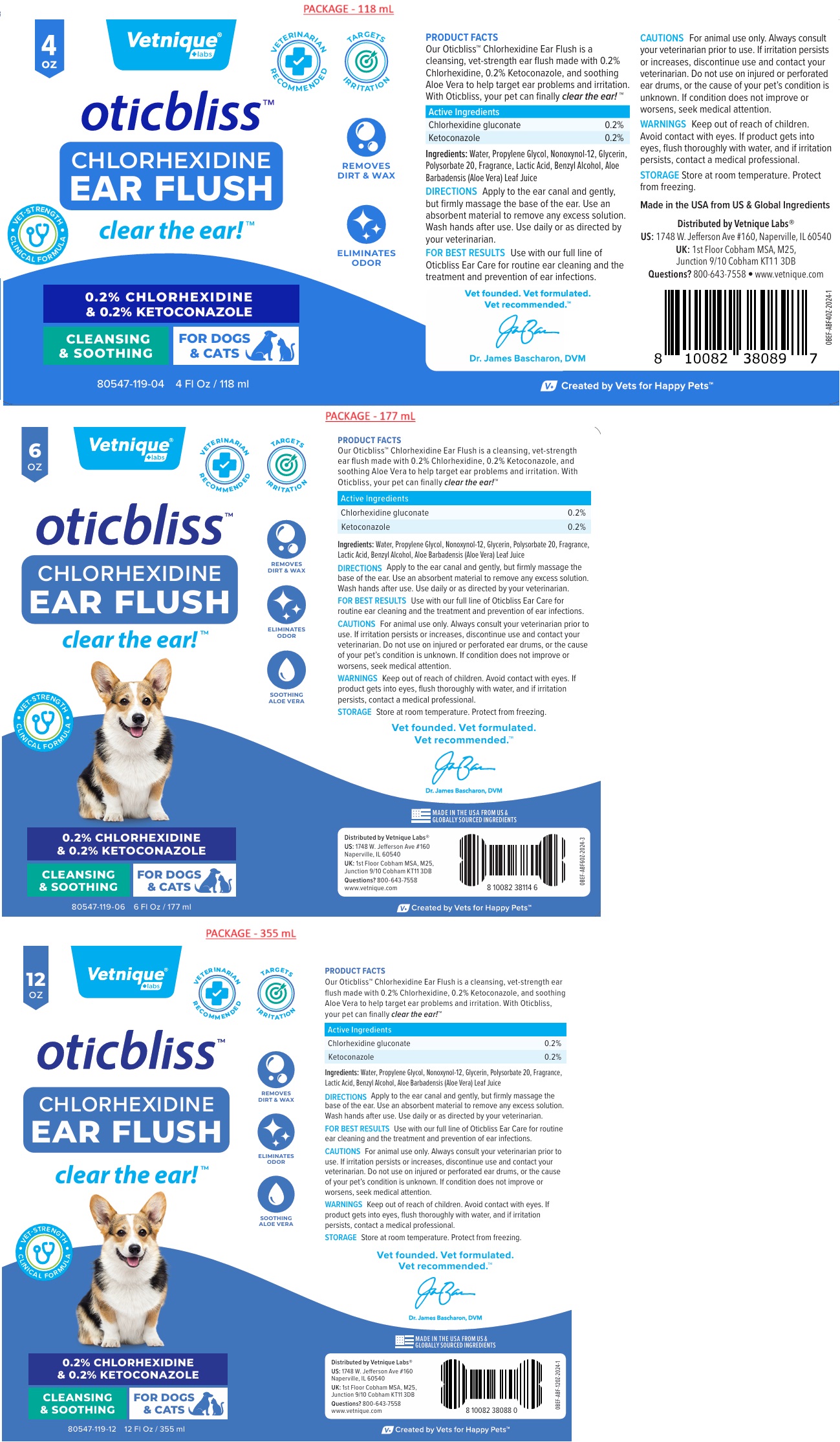 DRUG LABEL: oticbliss EAR FLUSH
NDC: 80547-119 | Form: SOLUTION
Manufacturer: Vetnique Labs LLC
Category: animal | Type: OTC ANIMAL DRUG LABEL
Date: 20241025

ACTIVE INGREDIENTS: CHLORHEXIDINE GLUCONATE 2 mg/1 mL; KETOCONAZOLE 2 mg/1 mL
INACTIVE INGREDIENTS: WATER; PROPYLENE GLYCOL; NONOXYNOL-12; GLYCERIN; POLYSORBATE 20; LACTIC ACID, UNSPECIFIED FORM; BENZYL ALCOHOL; ALOE VERA LEAF

oticbliss™ CHLORHEXIDINE EAR FLUSH

Active Ingredients

Chlorhexidine gluconate 0.2%
Ketoconazole 0.2%

INDICATIONS AND USAGE

PRODUCT FACTS
Our Oticbliss™ Chlorhexidine Ear Flush is a cleansing, vet-strength ear flush made with 0.2% Chlorhexidine, 0.2% Ketoconazole, and soothing Aloe Vera to help target ear problems and irritation. With Oticbliss, your pet can finally clear the ear!™

INACTIVE INGREDIENT

Ingredients: Water, Propylene Glycol, Nonoxynol-12, Glycerin, Polysorbate 20, Fragrance, Lactic Acid, Benzyl Alcohol, Aloe Barbadensis (Aloe Vera) Leaf Juice

DOSAGE AND ADMINISTRATION

DIRECTIONS Apply to the ear canal and gently, but firmly massage the base of the ear. Use an absorbent material to remove any excess solution. Wash hands after use. Use daily or as directed by your veterinarian.

FOR BEST RESULTS Use with our full line of Oticbliss Ear Care for routine ear cleaning and the treatment and prevention of ear infections.

PRECAUTIONS

CAUTIONS For animal use only. Always consult your veterinarian prior to use. If irritation persists or increases, discontinue use and contact your veterinarian. Do not use on injured or perforated ear drums, or the cause of your pet’s condition is unknown. If condition does not improve or worsens, seek medical attention.

WARNINGS

WARNINGS Keep out of reach of children. Avoid contact with eyes. If product gets into eyes, flush thoroughly with water, and if irritation persists, contact a medical professional.

STORAGE Store at room temperature. Protect from freezing.

clear the ear!™

• VET-STRENGTH • CLINICAL FORMULA

CLEANSING & SOOTHING

FOR DOGS & CATS

VETERINARIAN RECOMMENDED

TARGETS IRRITATION

REMOVES DIRT & WAX

ELIMINATES ODOR

SOOTHING ALOE VERA

Vet founded. Vet formulated.
Vet recommended.™

Dr. James Bascharon, DVM

Made in the USA from US & Global Ingredients

Distributed by Vetnique Labs®

US: 1748 W. Jefferson Ave #160, Naperville, IL 60540

UK: 1st Floor Cobham MSA, M25, Junction 9/10 Cobham KT11 3DB

Questions? 800-643-7558 • www.vetnique.com

V+ Created by Vets for Happy Pets™